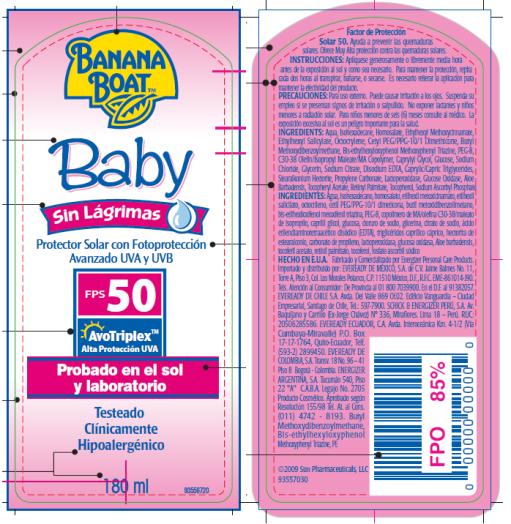 DRUG LABEL: Banana Boat Baby Sin Lagrimas SPF 50 Pump
NDC: 17630-2010 | Form: SPRAY
Manufacturer: Accra-Pac, Inc.
Category: otc | Type: HUMAN OTC DRUG LABEL
Date: 20100322

ACTIVE INGREDIENTS: HOMOSALATE 0.1 mL/1 mL; OCTINOXATE 0.075 mL/1 mL; OCTISALATE 0.05 mL/1 mL; OCTOCRYLENE 0.05 mL/1 mL; AVOBENZONE 0.03 mL/1 mL
INACTIVE INGREDIENTS: BEMOTRIZINOL; CAPRYLYL GLYCOL; SODIUM CHLORIDE; GLYCERIN; SODIUM CITRATE; EDETATE DISODIUM; MEDIUM-CHAIN TRIGLYCERIDES; PROPYLENE CARBONATE; GLUCOSE OXIDASE; ALOE VERA LEAF; .ALPHA.-TOCOPHEROL ACETATE, D-; VITAMIN A PALMITATE; SODIUM ASCORBYL PHOSPHATE

Banana Boat Baby Sin Lagrimas SPF 50 Pump Spray

ACTIVE INGREDIENTS:

Homosalate 0.1mL / 1mL

Octinoxate 0.075mL / 1mL

Octisalate 0.05mL / 1mL

Octocrylene 0.05mL / 1mL

Avobenzone 0.03mL / 1mL

INSTRUCCIONES:

Aplíquese generosamente o libremente media hora antes de la exposición al sol y como sea necesario. Para mantener la protección, repita cada dos horas al transpirar, bañarse, o secarse. Es necesario reiterar la aplicación para mantener la efectividad del producto.

PRECAUCIONES:

Para uso externo. Puede causar irritación a los ojos. Suspenda su empleo si se presentan signos de irritación o salpullido. No exponer lactantes y niños menores a radiación solar. Para niños menores de seis (6) meses consulte al médico. La exposición excesiva al sol es un peligro importante para la salud.

INGREDIENTS:

Aqua, Isohexadecane, Homosalate, Ethylhexyl Methoxycinnamate, Ethylhexyl Salicylate, Octocrylene, Cetyl PEG/PPG-10/1 Dimethicone, Butyl Methoxydibenzoylmethane, Bis-ethylhexyloxyphenol Methoxyphenyl Triazine, PEG-8, C30-38 Olefin/Isopropyl Maleate/MA Copolymer, Caprylyl Glycol, Glucose, Sodium Chloride, Glycerin, Sodium Citrate, Disodium EDTA, Caprylic/Capric Triglycerides, Stearalkonium Hectorite, Propylene Carbonate, Lactoperoxidase, Glucose Oxidase, Aloe Barbadensis, Tocopheryl Acetate, Retinyl Palmitate, Tocopherol, Sodium Ascorbyl Phosphate

INGREDIENTES:

Agua, isohexadecano, homosalato, etilhexil metoxicinamato, etilhexil salicilato, octocrileno, cetil PEG/PPG-10/1 dimeticona, butil metoxidibenzoilmetano, bis-etilhexiloxifenol metoxifenil triazina, PEG-8, copolímero de MA/olefina C30-38/maleato de isopropilo, caprilil glicol, glucosa, cloruro de sodio, glicerina, citrato de sodio, ácido etilendiaminotetraacético disódico (EDTA), triglicéridos caprílico cáprico, hectorita de estearalconio, carbonato de propileno, lactoperoxidasa, glucosa oxidasa, Aloe barbadensis, tocoferil acetato, retinil palmitato, tocoferol, fosfato ascorbil sódico

HECHO EN E.U.A. Fabricado y Comercializado por Energizer Personal Care Products. Importado y distribuido por: EVEREADY DE MÉXICO, S.A. de C.V. Jaime Balmes No. 11, Torre A, Piso 3, Col. Los Morales Polanco, C.P. 11510 México, D.F., R.F.C. EME-861014-J90. Tels. Atención al Consumidor: De Provincia al 01 800 7039900. En el D.F. al 91382057. EVEREADY DE CHILE S.A. Avda. Del Valle 869 Of.02. Edificio Vanguardia – Ciudad Empresarial, Santiago de Chile, Tel.: 597-7900. SCHICK & ENERGIZER PERÚ, S.A. Av. Baquíjano y Carrillo (Ex-Jorge Chávez) N° 336, Miraflores. Lima 18 – Perú. RUC: 20506285586. EVEREADY ECUADOR, C.A. Avda. Interoceánica Km. 4-1/2 (Vía Cumbaya-Miravalle) P.O. Box 17-17-1764, Quito-Ecuador, Telf. (593-2) 2899450. EVEREADY DE COLOMBIA, S.A. Transv. 18 No. 96 – 41 Piso 8 Bogotá - Colombia. ENERGIZER ARGENTINA, S.A. Tucumán 540, Piso 22 "A" C.A.B.A. Legajo No. 2705 Producto Cosmético. Aprobado según Resoluci_n 155/98 Tel. At. al Cons. (011) 4742 - 8193.

PRINCIPAL DISPLAY PANEL

Banana
BoatTM
Baby
Sin Lágrimas
Protector Solar con Fotoprotección
Avanzado UVA y UVB
FPS 50
AvoTriplexTM
Alta Protección UVA
Probado en el sol
y laboratorio
Testeado
Clínicamente
Hipoalergénico
180 ml